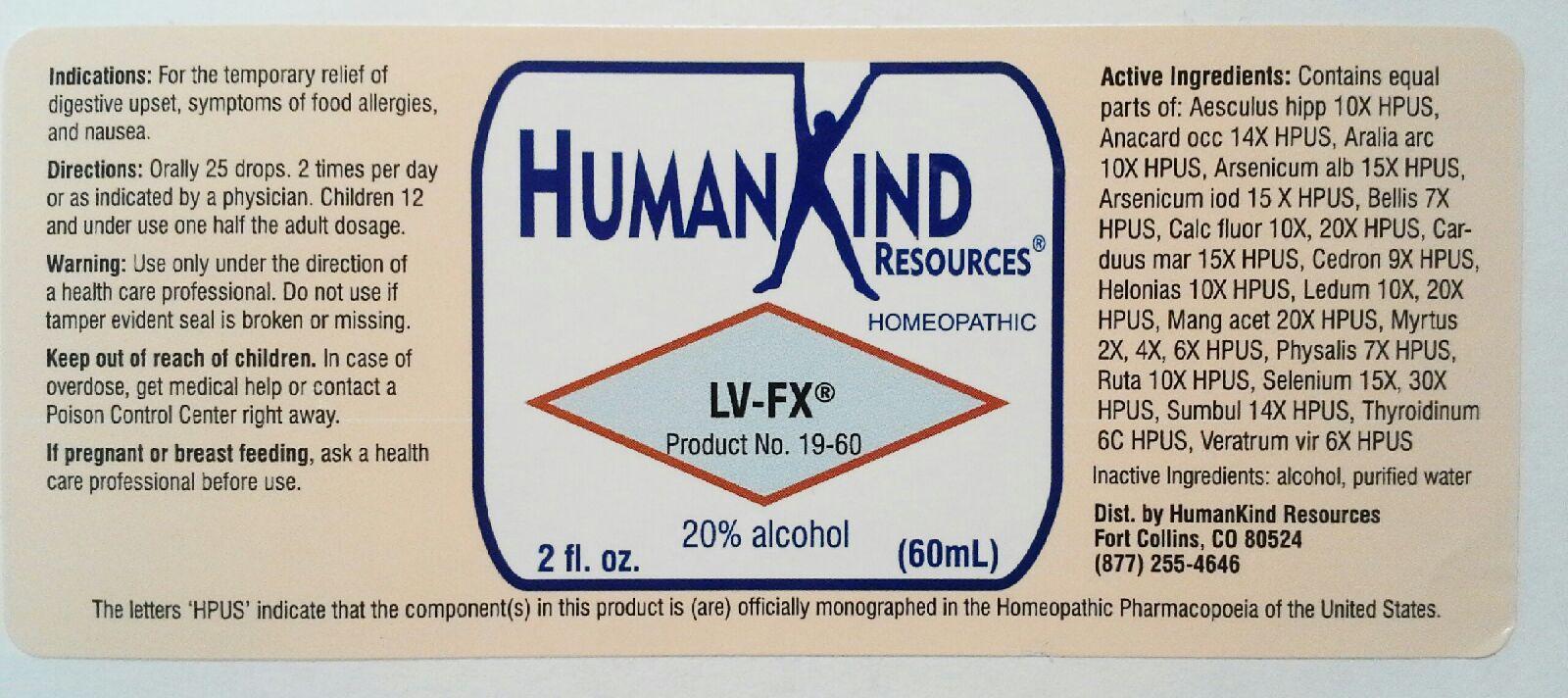 DRUG LABEL: LV-FX
NDC: 64616-097 | Form: LIQUID
Manufacturer: Vitality Works, Inc
Category: homeopathic | Type: HUMAN OTC DRUG LABEL
Date: 20251217

ACTIVE INGREDIENTS: HORSE CHESTNUT 10 [hp_X]/1 mL; ANACARDIUM OCCIDENTALE FRUIT 14 [hp_X]/1 mL; ARALIA RACEMOSA ROOT 10 [hp_X]/1 mL; ARSENIC TRIOXIDE 15 [hp_X]/1 mL; ARSENIC TRIIODIDE 15 [hp_X]/1 mL; BELLIS PERENNIS 7 [hp_X]/1 mL; CALCIUM FLUORIDE 20 [hp_X]/1 mL; MILK THISTLE 15 [hp_X]/1 mL; SIMABA CEDRON SEED 9 [hp_X]/1 mL; CHAMAELIRIUM LUTEUM ROOT 10 [hp_X]/1 mL; LEDUM PALUSTRE TWIG 20 [hp_X]/1 mL; MANGANESE ACETATE TETRAHYDRATE 20 [hp_X]/1 mL; MYRTUS COMMUNIS TOP 6 [hp_X]/1 mL; PHYSALIS ALKEKENGI FRUIT 7 [hp_X]/1 mL; RUTA GRAVEOLENS FLOWERING TOP 10 [hp_X]/1 mL; SELENIUM 30 [hp_X]/1 mL; FERULA SUMBUL ROOT 14 [hp_X]/1 mL; THYROID, UNSPECIFIED 6 [hp_C]/1 mL; VERATRUM VIRIDE ROOT 6 [hp_X]/1 mL
INACTIVE INGREDIENTS: ALCOHOL; WATER

LV-FX

LV-FX

Aesculus Hippocastanum 10X Carduus Marianus 15X Ruta Graveolens 10X

Anacardium Occidentale 14X Cedron 9X Selenium Metallicum 15X, 30X

Aralia Racemosa 10X Helonias Dioica 10X Sumbul 14X

Arsenicum Album 13X Ledum Palustre 10X, 20X Thyroidinum 6C

Arsenicum Iodatum 13X Manganum Aceticum 20X Veratrum Viride 6X

Bellis Perennis 7X Myrtus Communis 2X

Calcarea Fluorica 10X, 20X Physalis Alkekengi 5X

LV-FX

Acohol, Purified Water

LV-FX

Use only under the direction of a health care professional. Do not use if tamper evident seal is broken or missing.

LV-FX

Keep out of reach of children. In case of overdose, get medical help or contact Poison Control Center right away.

LV-FX

For the temporary relief of digestive upset, symptoms of food allergies and nausea.

LV-FX

Orally 25 drops, 2 times per day or as indicated by a physician. Children 12 and under use one half the adult dosage.

LV-FX

Aids in liver function.